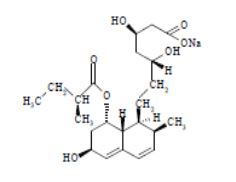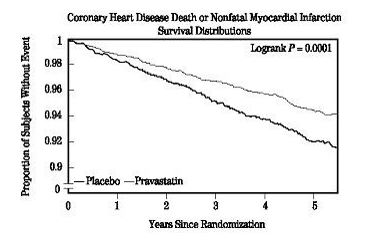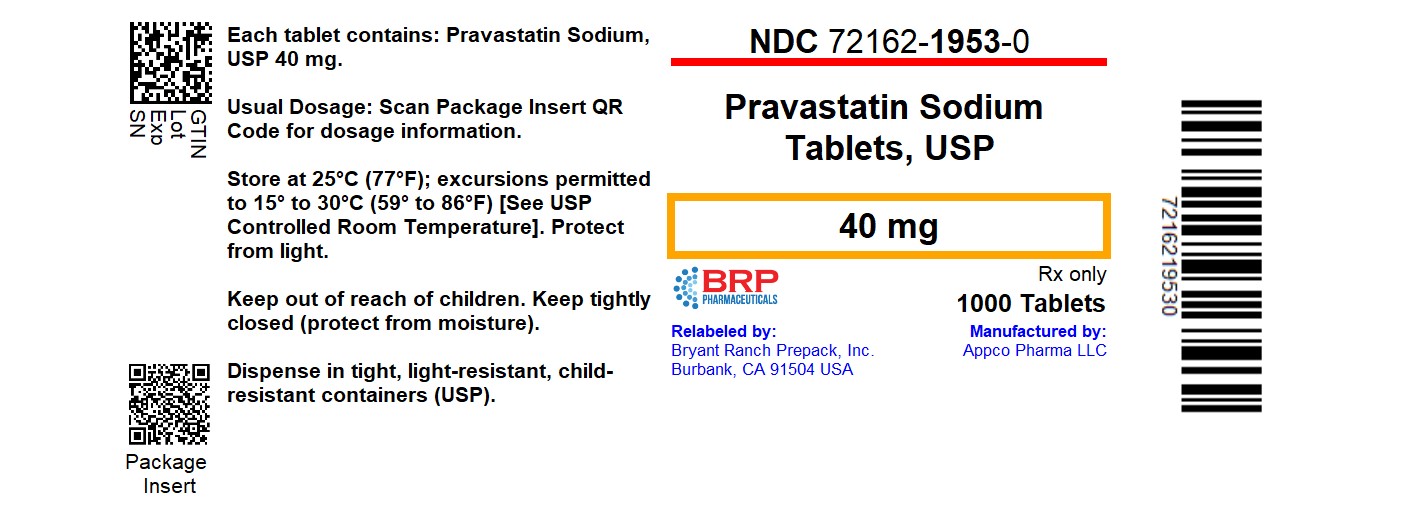 DRUG LABEL: PRAVASTATIN SODIUM
NDC: 72162-1953 | Form: TABLET
Manufacturer: Bryant Ranch Prepack
Category: prescription | Type: HUMAN PRESCRIPTION DRUG LABEL
Date: 20250519

ACTIVE INGREDIENTS: PRAVASTATIN SODIUM 40 mg/1 1
INACTIVE INGREDIENTS: CROSCARMELLOSE SODIUM; LACTOSE MONOHYDRATE; MAGNESIUM OXIDE; MAGNESIUM STEARATE; MICROCRYSTALLINE CELLULOSE; POVIDONE, UNSPECIFIED

HIGHLIGHTS OF PRESCRIBING INFORMATION

These highlights do not include all the information needed to use PRAVASTATIN SODIUM TABLETS safely and effectively. See full prescribing information for PRAVASTATIN SODIUM TABLETS.
PRAVASTATIN SODIUM tablets, for oral use
Initial U.S. Approval: 1991

RECENT MAJOR CHANGES

Warnins and Precautions
Immune-Mediated Necrotizing Myopathy (5.2) 09/2020

1 INDICATIONS AND USAGE

Pravastatin Sodium is an HMG-CoA reductase inhibitor (statin) indicated as an adjunctive therapy to diet to:

- Reduce the risk of MI, revascularization, and cardiovascular mortality in hypercholesterolemic patients without clinically evident CHD.(1.1)
- Reduce the risk of total mortality by reducing coronary death, MI, revascularization, stroke/TIA, and the progression of coronary atherosclerosis in patients with clinically evident CHD.(1.1)
- Reduce elevated Total-C, LDL-C, ApoB, and TG levels and to increase HDL C in patients with primary hypercholesterolemia and mixed dyslipidemia.(1.2)
- Reduce elevated serum TG levels in patients with hypertriglyceridemia.(1.2)
- Treat patients with primary dysbetalipoproteinemia who are not responding to diet.(1.2)
- Treat children and adolescent patients ages 8 years and older with heterozygous familial hypercholesterolemia after failing an adequate trial of diet therapy.(1.2)

Limitations of use:

- Pravastatin sodium has not been studied in Fredrickson Types I and V dyslipidemias.(1.3)

2 DOSAGE AND ADMINISTRATION

- Adults: the recommended starting dose is 40 mg once daily. Use 80 mg dose only for patients not reaching LDL-C goal with 40 mg. (2.2)
- Significant renal impairment: the recommended starting dose is pravastatin 10 mg once daily. (2.3)
- Children (ages 8 to 13 years, inclusive): the recommended starting dose is 20 mg once daily. (2.4)
- Adolescents (ages 14 to 18 years): the recommended starting dose is 40 mg once daily. (2.4)

3 DOSAGE FORMS AND STRENGTHS

- Tablets: 10 mg, 20 mg, 40 mg, 80 mg.(3)

4 CONTRAINDICATIONS

- Hypersensitivity to any component of this medication. (4.1, 6.2, 11)
- Active liver disease or unexplained, persistent elevations of serum transaminases. (4.2,5.3)
- Pregnancy (4.3, 8.1, 8.3)
- Lactation (4.4, 8.2)

5 WARNINGS AND PRECAUTIONS

- Skeletal muscle effects (e.g., myopathy and rhabdomyolysis): predisposing factors include advanced age (≥65), uncontrolled hypothyroidism, and renal impairment. Patients should be advised to promptly report to their physician any unexplained and/or persistent muscle pain, tenderness, or weakness. Pravastatin therapy should be discontinued if myopathy is diagnosed or suspected. (5.1, 8.5)
- Immune-Mediated Necrotizing Myopathy (IMNM): There have been rare reports of IMNM, an autoimmune myopathy, associated with statin use. IMNM is characterized by: proximal muscle weakness and elevated serum creatine kinase, which persist despite discontinuation of statin treatment, positive anti-HMG CoA reductase antibody, muscle biopsy showing necrotizing myopathy and improvement with immunosuppressive agents (5.2).
- Liver enzyme abnormalities: persistent elevations in hepatic transaminases can occur. Check liver enzyme tests before initiating therapy and as clinically indicated thereafter. (5.3)

6 ADVERSE REACTIONS

In short-term clinical trials, the most commonly reported adverse reactions (≥2% and > placebo) regardless of causality were: musculoskeletal pain, nausea/vomiting, upper respiratory infection, diarrhea, and headache.(6.1)

To report SUSPECTED ADVERSE REACTIONS, contact Biocon Pharma Inc. at 1-866-924-6266 or FDA at 1-800-FDA-1088 or www.fda.gov/medwatch.

7 DRUG INTERACTIONS

- Concomitant lipid-lowering therapies: use with fibrates or lipid-modifying doses (≥1 g/day) of niacin increases the risk of adverse skeletal muscle effects. Caution should be used when prescribing with Pravastatin Sodium.(7)
- Cyclosporine: combination increases exposure. Limit pravastatin to 20 mg once daily. (2.6, 7.1)
- Clarithromycin: combination increases exposure. Limit pravastatin to 40 mg once daily.(2.7, 7.2)

FULL PRESCRIBING INFORMATION

1 INDICATIONS AND USAGE

Therapy with lipid-altering agents should be only one component of multiple risk factor intervention in individuals at significantly increased risk for atherosclerotic vascular disease due to hypercholesterolemia. Drug therapy is indicated as an adjunct to diet when the response to a diet restricted in saturated fat and cholesterol and other nonpharmacologic measures alone has been inadequate.

1.1 Prevention of Cardiovascular Disease

In hypercholesterolemic patients without clinically evident coronary heart disease (CHD), Pravastatin Sodium is indicated to:

- reduce the risk of myocardial infarction (MI).
- reduce the risk of undergoing myocardial revascularization procedures.
- reduce the risk of cardiovascular mortality with no increase in death from non-cardiovascular causes.

In patients with clinically evident CHD, Pravastatin Sodium is indicated to:

- reduce the risk of total mortality by reducing coronary death.
- reduce the risk of MI
- reduce the risk of undergoing myocardial revascularization procedures.
- reduce the risk of stroke and stroke/transient ischemic attack (TIA).
- slow the progression of coronary atherosclerosis.

1.2 Hyperlipidemia

Pravastatin Sodium is indicated:

- as an adjunct to diet to reduce elevated total cholesterol (Total-C), low-density lipoprotein cholesterol (LDL-C), apolipoprotein B (ApoB), and triglyceride (TG) levels and to increase high-density lipoprotein cholesterol (HDL-C) in patients with primary hypercholesterolemia and mixed dyslipidemia (Fredrickson Types IIa and IIb).^1
- as an adjunct to diet for the treatment of patients with elevated serum TG levels (Fredrickson Type IV).
- for the treatment of patients with primary dysbetalipoproteinemia (Fredrickson Type III) who do not respond adequately to diet.
- as an adjunct to diet and lifestyle modification for treatment of heterozygous familial hypercholesterolemia (HeFH) in children and adolescent patients ages 8 years and older if after an adequate trial of diet the following findings are present:

a. LDL-C remains ≥190 mg/dL or

b. LDL-C remains ≥160 mg/dL and:

- there is a positive family history of premature cardiovascular disease (CVD) or
- two or more other CVD risk factors are present in the patient.

1.3 Limitations of Use

Pravastatin Sodium has not been studied in conditions where the major lipoprotein abnormality is elevation of chylomicrons (Fredrickson Types I and V).

2 DOSAGE AND ADMINISTRATION

2.1 General Dosing Information

The patient should be placed on a standard cholesterol-lowering diet before receiving Pravastatin Sodium and should continue on this diet during treatment with Pravastatin Sodium [see NCEP Treatment Guidelines for details on dietary therapy].

2.2 Adult Patients

The recommended starting dose is 40 mg once daily. If a daily dose of 40 mg does not achieve desired cholesterol levels, 80 mg once daily is recommended. Pravastatin Sodium can be administered orally as a single dose at any time of the day, with or without food. Since the maximal effect of a given dose is seen within 4 weeks, periodic lipid determinations should be performed at this time and dosage adjusted according to the patient’s response to therapy and established treatment guidelines.

2.3 Patients with Renal Impairment

In patients with severe renal impairment, a starting dose of 10 mg pravastatin daily is recommended.

2.4 Pediatric Patients

Children (Ages 8 to 13 Years, Inclusive)

The recommended dose is 20 mg once daily in children 8 to 13 years of age. Doses greater than 20 mg have not been studied in this patient population.

Adolescents (Ages 14 to 18 Years)

The recommended starting dose is 40 mg once daily in adolescents 14 to 18 years of age. Doses greater than 40 mg have not been studied in this patient population.

Children and adolescents treated with pravastatin should be reevaluated in adulthood and appropriate changes made to their cholesterol-lowering regimen to achieve adult goals for LDL-C [see Indications and Usage (1.2)].

2.5 Concomitant Lipid-Altering Therapy

Pravastatin Sodium may be used with bile acid resins. When administering a bile-acid-binding resin (e.g., cholestyramine, colestipol) and pravastatin, Pravastatin Sodium should be given either 1 hour or more before or at least 4 hours following the resin. [See Clinical Pharmacology (12.3)]

2.6 Dosage in Patients Taking Cyclosporine

In patients taking immunosuppressive drugs such as cyclosporine concomitantly with pravastatin, therapy should begin with 10 mg of pravastatin sodium once-a-day at bedtime and titration to higher doses should be done with caution. Most patients treated with this combination received a maximum pravastatin sodium dose of 20 mg/day. In patients taking cyclosporine, therapy should be limited to 20 mg of pravastatin sodium once daily [see Warnings and Precautions (5.1) and Drug Interactions (7.1)].

2.7 Dosage in Patients Taking Clarithromycin

In patients taking clarithromycin, therapy should be limited to 40 mg of pravastatin sodium once daily [see Drug Interactions (7.2)].

3 DOSAGE FORMS AND STRENGTHS

Pravastatin Sodium Tablets, USP are supplied as:

10 mg tablets: White to off-white, Rectangular-shaped, biconvex tablets, debossed with “B 10” on one side and plain on other side.

20 mg tablets: White to off-white, Rectangular-shaped, biconvex tablets, debossed with “B 20” on one side and plain on other side.

40 mg tablets: White to off-white, Rectangular-shaped, biconvex tablets, debossed with “B 40” on one side and plain on other side.

80 mg tablets: White to off-white, Oval-shaped, biconvex tablets, debossed with “B 80” on one side and plain on other side.

4 CONTRAINDICATIONS

4.1 Hypersensitivity

Hypersensitivity to any component of this medication.

4.2 Liver

Active liver disease or unexplained, persistent elevations of serum transaminases [see Warnings and Precautions (5.3) ].

4.3 Pregnancy

Atherosclerosis is a chronic process and discontinuation of lipid-lowering drugs during pregnancy should have little impact on the outcome of long-term therapy of primary hypercholesterolemia. Cholesterol and other products of cholesterol biosynthesis are essential components for fetal development (including synthesis of steroids and cell membranes). Since statins decrease cholesterol synthesis and possibly the synthesis of other biologically active substances derived from cholesterol, they are contraindicated during pregnancy and in nursing mothers. PRAVASTATIN SHOULD BE ADMINISTERED TO WOMEN OF CHILDBEARING AGE ONLY WHEN SUCH PATIENTS ARE HIGHLY UNLIKELY TO CONCEIVE AND HAVE BEEN INFORMED OF THE POTENTIAL HAZARDS. If the patient becomes pregnant while taking this class of drug, therapy should be discontinued immediately and the patient apprised of the potential hazard to the fetus [see Use in Specific Populations (8.1,8.3)].

4.4 Lactation

Pravastatin is present in human milk. Because statins have the potential for serious adverse reactions in nursing infants, women who require Pravastatin Sodium treatment should not breastfeed their infants [see Use in Specific Populations (8.2)].

5 WARNINGS AND PRECAUTIONS

5.1 Skeletal Muscle

Rare cases of rhabdomyolysis with acute renal failure secondary to myoglobinuria have been reported with pravastatin and other drugs in this class. A history of renal impairment may be a risk factor for the development of rhabdomyolysis. Such patients merit closer monitoring for skeletal muscle effects.

Uncomplicated myalgia has also been reported in pravastatin-treated patients [see Adverse Reactions (6)]. Myopathy, defined as muscle aching or muscle weakness in conjunction with increases in creatine phosphokinase (CPK) values to greater than 10 times the ULN, was rare (<0.1%) in pravastatin clinical trials. Myopathy should be considered in any patient with diffuse myalgias, muscle tenderness or weakness, and/or marked elevation of CPK. Predisposing factors include advanced age (65), uncontrolled hypothyroidism, and renal impairment.

All patients should be advised to promptly report to their physician unexplained muscle pain, tenderness, or weakness, particularly if accompanied by malaise or fever or if muscle signs and symptoms persist after discontinuing Pravastatin Sodium.

Pravastatin therapy should be discontinued if markedly elevated CPK levels occur or myopathy is diagnosed or suspected. Pravastatin therapy should also be temporarily withheld in any patient experiencing an acute or serious condition predisposing to the development of renal failure secondary to rhabdomyolysis, e.g., sepsis; hypotension; major surgery; trauma; severe metabolic, endocrine, or electrolyte disorders; or uncontrolled epilepsy.

The risk of myopathy during treatment with statins is increased with concurrent therapy with either erythromycin, cyclosporine, niacin, or fibrates. However, neither myopathy nor significant increases in CPK levels have been observed in 3 reports involving a total of 100 post-transplant patients (24 renal and 76 cardiac) treated for up to 2 years concurrently with pravastatin 10 to 40 mg and cyclosporine. Some of these patients also received other concomitant immunosuppressive therapies. Further, in clinical trials involving small numbers of patients who were treated concurrently with pravastatin and niacin, there were no reports of myopathy. Also, myopathy was not reported in a trial of combination pravastatin (40 mg/day) and gemfibrozil (1200 mg/day), although 4 of 75 patients on the combination showed marked CPK elevations versus 1 of 73 patients receiving placebo. There was a trend toward more frequent CPK elevations and patient withdrawals due to musculoskeletal symptoms in the group receiving combined treatment as compared with the groups receiving placebo, gemfibrozil, or pravastatin monotherapy. The use of fibrates alone may occasionally be associated with myopathy. The benefit of further alterations in lipid levels by the combined use of Pravastatin Sodium with fibrates should be carefully weighed against the potential risks of this combination.

Cases of myopathy, including rhabdomyolysis, have been reported with pravastatin coadministered with colchicine, and caution should be exercised when prescribing pravastatin with colchicine [see Drug Interactions (7.3)].

5.2 Immune-Mediated Necrotizing Myopathy

There have been rare reports of immune-mediated necrotizing myopathy (IMNM), an autoimmune myopathy, associated with statin use. IMNM is characterized by: proximal muscle weakness and elevated serum creatine kinase, which persist despite discontinuation of statin treatment; positive anti-HMG CoA reductase antibody; muscle biopsy showing necrotizing myopathy; and improvement with immunosuppressive agents. Additional neuromuscular and serologic testing may be necessary. Treatment with immunosuppressive agents may be required. Consider risk of IMNM carefully prior to initiation of a different statin. If therapy is initiated with a different statin, monitor for signs and symptoms of IMNM.

5.3 Liver

Statins, like some other lipid-lowering therapies, have been associated with biochemical abnormalities of liver function. In 3 long-term (4.8-5.9 years), placebo-controlled clinical trials (WOS, LIPID, CARE), 19,592 subjects (19,768 randomized) were exposed to pravastatin or placebo [see Clinical Studies (14)]. In an analysis of serum transaminase values (ALT, AST), incidences of marked abnormalities were compared between the pravastatin and placebo treatment groups; a marked abnormality was defined as a post-treatment test value greater than 3 times the ULN for subjects with pretreatment values less than or equal to the ULN, or 4 times the pretreatment value for subjects with pretreatment values greater than the ULN but less than 1.5 times the ULN. Marked abnormalities of ALT or AST occurred with similar low frequency (≤1.2%) in both treatment groups. Overall, clinical trial experience showed that liver function test abnormalities observed during pravastatin therapy were usually asymptomatic, not associated with cholestasis, and did not appear to be related to treatment duration. In a 320patient placebo-controlled clinical trial, subjects with chronic (>6 months) stable liver disease, due primarily to hepatitis C or non-alcoholic fatty liver disease, were treated with 80 mg pravastatin or placebo for up to 9 months. The primary safety endpoint was the proportion of subjects with at least one ALT ≥2 times the ULN for those with normal ALT (≤ ULN) at baseline or a doubling of the baseline ALT for those with elevated ALT (> ULN) at baseline. By Week 36, 12 out of 160 (7.5%) subjects treated with pravastatin met the prespecified safety ALT endpoint compared to 20 out of 160 (12.5%) subjects receiving placebo. Conclusions regarding liver safety are limited since the study was not large enough to establish similarity between groups (with 95% confidence) in the rates of ALT elevation.

It is recommended that liver function tests be performed prior to the initiation of therapy and when clinically indicated.

Active liver disease or unexplained persistent transaminase elevations are contraindications to the use of pravastatin [see Contraindications (4.2)]. Caution should be exercised when pravastatin is administered to patients who have a recent (<6 months) history of liver disease, have signs that may suggest liver disease (e.g., unexplained aminotransferase elevations, jaundice), or are heavy users of alcohol.

There have been rare postmarketing reports of fatal and non-fatal hepatic failure in patients taking statins, including pravastatin. If serious liver injury with clinical symptoms and/or hyperbilirubinemia or jaundice occurs during treatment with Pravastatin Sodium, promptly interrupt therapy. If an alternate etiology is not found do not restart Pravastatin Sodium.

5.4 Endocrine Function

Statins interfere with cholesterol synthesis and lower circulating cholesterol levels and, as such, might theoretically blunt adrenal or gonadal steroid hormone production. Results of clinical trials with pravastatin in males and post-menopausal females were inconsistent with regard to possible effects of the drug on basal steroid hormone levels. In a study of 21 males, the mean testosterone response to human chorionic gonadotropin was significantly reduced (p<0.004) after 16 weeks of treatment with 40 mg of pravastatin. However, the percentage of patients showing a ≥50% rise in plasma testosterone after human chorionic gonadotropin stimulation did not change significantly after therapy in these patients. The effects of statins on spermatogenesis and fertility have not been studied in adequate numbers of patients. The effects, if any, of pravastatin on the pituitary- gonadal axis in pre-menopausal females are unknown. Patients treated with pravastatin who display clinical evidence of endocrine dysfunction should be evaluated appropriately. Caution should also be exercised if a statin or other agent used to lower cholesterol levels is administered to patients also receiving other drugs (e.g., ketoconazole, spironolactone, cimetidine) that may diminish the levels or activity of steroid hormones.

In a placebo-controlled study of 214 pediatric patients with HeFH, of which 106 were treated with pravastatin (20 mg in the children aged 8-13 years and 40 mg in the adolescents aged 14-18 years) for 2 years, there were no detectable differences seen in any of the endocrine parameters (ACTH, cortisol, DHEAS, FSH, LH, TSH, estradiol [girls] or testosterone [boys]) relative to placebo. There were no detectable differences seen in height and weight changes, testicular volume changes, or Tanner score relative to placebo.

6 ADVERSE REACTIONS

Pravastatin is generally well tolerated; adverse reactions have usually been mild and transient. In 4-month-long placebo-controlled trials, 1.7% of pravastatin-treated patients and 1.2% of placebo-treated patients were discontinued from treatment because of adverse experiences attributed to study drug therapy; this difference was not statistically significant.

6.1 Adverse Clinical Events

Short-Term Controlled Trials

In the Pravastatin Sodium placebo-controlled clinical trials database of 1313 patients (age range 20-76 years, 32.4% women, 93.5% Caucasians, 5% Blacks, 0.9% Hispanics, 0.4% Asians, 0.2% Others) with a median treatment duration of 14 weeks, 3.3% of patients on Pravastatin Sodium and 1.2% patients on placebo discontinued due to adverse events regardless of causality. The most common adverse reactions that led to treatment discontinuation and occurred at an incidence greater than placebo were: liver function test increased, nausea, anxiety/depression, and dizziness.

All adverse clinical events (regardless of causality) reported in ≥2% of pravastatin-treated patients in placebo-controlled trials of up to 8 months duration are identified in Table 1:

Table 1: Adverse Events in ≥2% of Patients Treated with Pravastatin 5 to 40 mg and at an Incidence Greater Than Placebo in Short-Term Placebo-Controlled Trials (% of patients)
Body System/Event | 5 mg N=100 | 10 mg N=153 | 20 mg N=478 | 40 mg N=171 | Any Dose N=902 | Placebo N=411
Cardiovascular Angina Pectoris | 5.0 | 4.6 | 4.8 | 3.5 | 4.5 | 3.4
Dermatologic Rash | 3.0 | 2.6 | 6.7 | 1.2 | 4.5 | 1.4
Gastrointestinal Nausea/Vomiting Diarrhea Flatulence Dyspepsia/Heartburn Abdominal Distension | 4.0 8.0 2.0 0.0 2.0 | 5.9 8.5 3.3 3.3 3.3 | 10.5 6.5 4.6 3.6 2.1 | 2.3 4.7 0.0 0.6 0.6 | 7.4 6.7 3.2 2.5 2.0 | 7.1 5.6 4.4 2.7 2.4
General Fatigue Chest Pain Influenza | 4.0 4.0 4.0 | 1.3 1.3 2.6 | 5.2 3.3 1.9 | 0.0 1.2 0.6 | 3.4 2.7 2.0 | 3.9 1.9 0.7
Musculoskeletal Musculoskeletal Pain Myalgia | 13.0 1.0 | 3.9 2.6 | 13.2 2.9 | 5.3 1.2 | 10.1 2.3 | 10.2 1.2
Nervous System Headache Dizziness | 5.0 4.0 | 6.5 1.3 | 7.5 5.2 | 3.5 0.6 | 6.3 3.5 | 4.6 3.4
Respiratory Pharyngitis Upper Respiratory Infection Rhinitis Cough | 2.0 6.0 7.0 4.0 | 4.6 9.8 5.2 1.3 | 1.5 5.2 3.8 3.1 | 1.2 4.1 1.2 1.2 | 2.0 5.9 3.9 2.5 | 2.7 5.8 4.9 1.7
Investigation ALT Increased g-GT Increased CPK Increased | 2.0 3.0 5.0 | 2.0 2.6 1.3 | 4.0 2.1 5.2 | 1.2 0.6 2.9 | 2.9 2.0 4.1 | 1.2 1.2 3.6

The safety and tolerability of Pravastatin Sodium at a dose of 80 mg in 2 controlled trials with a mean exposure of 8.6 months was similar to that of Pravastatin Sodium at lower doses except that 4 out of 464 patients taking 80 mg of pravastatin had a single elevation of CK >10 times ULN compared to 0 out of 115 patients taking 40 mg of pravastatin.

Long-Term Controlled Morbidity and Mortality Trials

In the Pravastatin Sodium placebo-controlled clinical trials database of 21,483 patients (age range 24-75 years, 10.3% women, 52.3% Caucasians, 0.8% Blacks, 0.5% Hispanics, 0.1% Asians, 0.1% Others, 46.1% Not Recorded) with a median treatment duration of 261 weeks, 8.1% of patients on Pravastatin Sodium and 9.3% patients on placebo discontinued due to adverse events regardless of causality.

Adverse event data were pooled from 7 double-blind, placebo-controlled trials (West of Scotland Coronary Prevention Study [WOS]; Cholesterol and Recurrent Events study [CARE]; Long-term Intervention with Pravastatin in Ischemic Disease study [LIPID]; Pravastatin Limitation of Atherosclerosis in the Coronary Arteries study [PLAC I]; Pravastatin, Lipids and Atherosclerosis in the Carotids study [PLAC II]; Regression Growth Evaluation Statin Study [REGRESS]; and Kuopio Atherosclerosis Prevention Study [KAPS]) involving a total of 10,764 patients treated with pravastatin 40 mg and 10,719 patients treated with placebo. The safety and tolerability profile in the pravastatin group was comparable to that of the placebo group. Patients were exposed to pravastatin for a mean of 4.0 to 5.1 years in WOS, CARE, and LIPID and 1.9 to 2.9 years in PLAC I, PLAC II, KAPS, and REGRESS. In these long-term trials, the most common reasons for discontinuation were mild, non-specific gastrointestinal complaints. Collectively, these 7 trials represent 47,613 patient-years of exposure to pravastatin. All clinical adverse events (regardless of causality) occurring in ≥2% of patients treated with pravastatin in these studies are identified in Table 2.

Table 2: Adverse Events in ≥2% of Patients Treated with Pravastatin 40 mg and at an Incidence Greater Than Placebo in Long-Term Placebo- Controlled Trials
Body System/Event | Pravastatin (N=10,764) % of patients | Placebo (N=10,719) % of patients
Dermatologic Rash (including dermatitis) | 7.2 | 7.1
General Edema Fatigue Chest Pain Fever Weight Gain Weight Loss | 3.0 8.4 10.0 2.1 3.8 3.3 | 2.7 7.8 9.8 1.9 3.3 2.8
Musculoskeletal Musculoskeletal Pain Muscle Cramp Musculoskeletal Traumatism | 24.9 5.1 10.2 | 24.4 4.6 9.6
Nervous System Dizziness Sleep Disturbance Anxiety/Nervousness Paresthesia | 7.3 3.0 4.8 3.2 | 6.6 2.4 4.7 3.0
Renal/Genitourinary Urinary Tract Infection | 2.7 | 2.6
Respiratory Upper Respiratory Tract Infection Cough Influenza Pulmonary Infection Sinus Abnormality Tracheobronchitis | 21.2 8.2 9.2 3.8 7.0 3.4 | 20.2 7.4 9.0 3.5 6.7 3.1
Special Senses Vision Disturbance (includes blurred vision, diplopia) | 3.4 | 3.3
Infections Viral Infection | 3.2 | 2.9

In addition to the events listed above in the long-term trials table, events of probable, possible, or uncertain relationship to study drug that occurred in <2.0% of pravastatin-treated patients in the long-term trials included the following:

Dermatologic: scalp hair abnormality (including alopecia), urticaria.

Endocrine/Metabolic: sexual dysfunction, libido change.

General: flushing.

Immunologic: allergy, edema head/neck.

Musculoskeletal: muscle weakness.

Nervous System: vertigo, insomnia, memory impairment, neuropathy (including peripheral neuropathy).

Special Senses: taste disturbance.

6.2 Postmarketing Experience

In addition to the events reported above, as with other drugs in this class, the following events have been reported during postmarketing experience with Pravastatin Sodium, regardless of causality assessment:

Musculoskeletal: myopathy, rhabdomyolysis, tendon disorder, polymyositis.

There have been rare reports of immune-mediated necrotizing myopathy associated with statin use [see Warnings and Precautions (5.2) ].

Nervous System: dysfunction of certain cranial nerves (including alteration of taste, impairment of extraocular movement, facial paresis), peripheral nerve palsy.

There have been rare postmarketing reports of cognitive impairment (e.g., memory loss, forgetfulness, amnesia, memory impairment, confusion) associated with statin use. These cognitive issues have been reported for all statins. The reports are generally nonserious, and reversible upon statin discontinuation, with variable times to symptom onset (1 day to years) and symptom resolution (median of 3 weeks).

Hypersensitivity: anaphylaxis, angioedema, lupus erythematosus-like syndrome, polymyalgia rheumatica, dermatomyositis, vasculitis, purpura, hemolytic anemia, positive ANA, ESR increase, arthritis, arthralgia, asthenia, photosensitivity, chills, malaise, toxic epidermal necrolysis, erythema multiforme (including Stevens-Johnson syndrome).

Gastrointestinal: abdominal pain, constipation, pancreatitis, hepatitis (including chronic active hepatitis), cholestatic jaundice, fatty change in liver, cirrhosis, fulminant hepatic necrosis, hepatoma, fatal and non-fatal hepatic failure.

Dermatologic: a variety of skin changes (e.g., nodules, discoloration, dryness of mucous membranes, changes to hair/nails).

Renal: urinary abnormality (including dysuria, frequency, nocturia).

Respiratory: dyspnea, interstitial lung disease.

Psychiatric: nightmare.

Reproductive: gynecomastia.

Laboratory Abnormalities: liver function test abnormalities, thyroid function abnormalities.

6.3 Laboratory Test Abnormalities

Increases in ALT, AST values and CPK have been observed [see Warnings and Precautions (5.1, 5.3) ].

Transient, asymptomatic eosinophilia has been reported. Eosinophil counts usually returned to normal despite continued therapy. Anemia, thrombocytopenia, and leukopenia have been reported with statins

6.4 Pediatric Patients

In a 2-year, double-blind, placebo-controlled study involving 100 boys and 114 girls with HeFH (n=214; age range 8-18.5 years, 53% female, 95% Caucasians, <1% Blacks, 3% Asians, 1% Other), the safety and tolerability profile of pravastatin was generally similar to that of placebo. [See Warnings and Precautions (5.4), Use in Specific Populations (8.4), and Clinical Pharmacology (12.3).]

7 DRUG INTERACTIONS

For the concurrent therapy of either cyclosporine, fibrates, niacin (nicotinic acid), or erythromycin, the risk of myopathy increases [see Warnings and Precautions (5.1) and Clinical Pharmacology (12.3)].

7.1 Cyclosporine

The risk of myopathy/rhabdomyolysis is increased with concomitant administration of cyclosporine. Limit pravastatin to 20 mg once daily for concomitant use with cyclosporine [see Dosage and Administration (2.6), Warnings and Precautions (5.1), and Clinical Pharmacology (12.3)].

7.2 Clarithromycin and Other Macrolide Antibiotics

The risk of myopathy/rhabdomyolysis is increased with concomitant administration of clarithromycin. Limit pravastatin to 40 mg once daily for concomitant use with clarithromycin [see Dosage and Administration (2.7), Warnings and Precautions (5.1), and Clinical Pharmacology (12.3)].

Other macrolides (e.g., erythromycin and azithromycin) have the potential to increase statin exposures while used in combination. Pravastatin should be used cautiously with macrolide antibiotics due to a potential increased risk of myopathies.

7.3 Colchicine

The risk of myopathy/rhabdomyolysis is increased with concomitant administration of colchicine [see Warnings and Precautions (5.1)].

7.4 Gemfibrozil

Due to an increased risk of myopathy/rhabdomyolysis when HMG-CoA reductase inhibitors are coadministered with gemfibrozil, concomitant administration of Pravastatin Sodium with gemfibrozil should be avoided [see Warnings and Precautions (5.1)].

7.5 Other Fibrates

Because it is known that the risk of myopathy during treatment with HMG-CoA reductase inhibitors is increased with concurrent administration of other fibrates, Pravastatin Sodium should be administered with caution when used concomitantly with other fibrates [see Warnings and Precautions (5.1)].

7.6 Niacin

The risk of skeletal muscle effects may be enhanced when pravastatin is used in combination with niacin; a reduction in Pravastatin Sodium dosage should be considered in this setting [see Warnings and Precautions (5.1)].

8 USE IN SPECIFIC POPULATIONS

8.1 Pregnancy

Risk Summary

Pravastatin Sodium is contraindicated for use in pregnant woman because of the potential for fetal harm. As safety in pregnant women has not been established and there is no apparent benefit to therapy with Pravastatin Sodium during pregnancy, Pravastatin Sodium should be immediately discontinued as soon as pregnancy is recognized [see Contraindications (4.3)]. Limited published data on the use of Pravastatin Sodium in pregnant women are insufficient to determine a drug-associated risk of major congenital malformations or miscarriage. In animal reproduction studies, no evidence of fetal malformations was seen in rabbits or rats exposed to 10 times to 120 times, respectively, the maximum recommended human dose (MRHD) of 80 mg/day. Fetal skeletal abnormalities, offspring mortality, and developmental delays occurred when pregnant rats were administered 10 times to 12 times the MRHD during organogenesis to parturition [see Data]. Advise pregnant women of the potential risk to a fetus.

The estimated background risk of major birth defects and miscarriage for the indicated population is unknown. In the U.S. general population, the estimated background risk of major birth defects and miscarriage in clinically recognized pregnancies is 2-4% and 15-20%, respectively.

Data

Human Data

Limited published data on pravastatin have not shown an increased risk of major congenital malformations or miscarriage.

Rare reports of congenital anomalies have been received following intrauterine exposure to other statins. In a review^2 of approximately 100 prospectively followed pregnancies in women exposed to simvastatin or lovastatin, the incidences of congenital anomalies, spontaneous abortions, and fetal deaths/stillbirths did not exceed what would be expected in the general population. The number of cases is adequate to exclude a ≥3 to 4-fold increase in congenital anomalies over the background incidence. In 89% of the prospectively followed pregnancies, drug treatment was initiated prior to pregnancy and was discontinued at some point in the first trimester when pregnancy was identified.

Animal Data

Embryofetal and neonatal mortality was observed in rats given pravastatin during the period of organogenesis or during organogenesis continuing through weaning. In pregnant rats given oral gavage doses of 4, 20, 100, 500, and 1000 mg/kg/day from gestation days 7 through 17 (organogenesis) increased mortality of offspring and increased cervical rib skeletal anomalies were observed at ≥100 mg/kg/day systemic exposure, 10 times the human exposure at 80 mg/day MRHD based on body surface area (mg/m^2).

In other studies, no teratogenic effects were observed when pravastatin was dosed orally during organogenesis in rabbits (gestation days 6 through 18) up to 50 mg/kg/day or in rats (gestation days 7 through 17) up to 1000 mg/kg/day. Exposures were 10 times (rabbit) or 120 times (rat) the human exposure at 80 mg/day MRHD based on body surface area (mg/m^2).

In pregnant rats given oral gavage doses of 10, 100, and 1000 mg/kg/day from gestation day 17 through lactation day 21 (weaning), increased mortality of offspring and developmental delays were observed at ≥100 mg/kg/day systemic exposure, corresponding to 12 times the human exposure at 80 mg/day MRHD, based on body surface area (mg/m^2).

In pregnant rats, pravastatin crosses the placenta and is found in fetal tissue at 30% of the maternal plasma levels following administration of a single dose of 20 mg/day orally on gestation day 18, which corresponds to exposure 2 times the MRHD of 80 mg daily based on body surface area (mg/m^2). In lactating rats, up to 7 times higher levels of pravastatin are present in the breast milk than in the maternal plasma, which corresponds to exposure 2 times the MRHD of 80 mg/day based on body surface area (mg/m^2).

8.2 Lactation

Risk Summary

Pravastatin use is contraindicated during breastfeeding [see Contraindications (4.4)]. Based on one lactation study in published literature, pravastatin is present in human milk. There is no available information on the effects of the drug on the breastfed infant or the effects of the drug on milk production. Because of the potential for serious adverse reactions in a breastfed infant, advise patients that breastfeeding is not recommended during treatment with Pravastatin Sodium.

8.3 Females and Males of Reproductive Potential

Contraception

Females

Pravastatin Sodium may cause fetal harm when administered to a pregnant woman [see Use in Specific Populations (8.1)]. Advise females of reproductive potential to use effective contraception during treatment with Pravastatin Sodium.

8.4 Pediatric Use

The safety and effectiveness of Pravastatin Sodium in children and adolescents from 8 to 18 years of age have been evaluated in a placebo-controlled study of 2 years duration. Patients treated with pravastatin had an adverse experience profile generally similar to that of patients treated with placebo with influenza and headache commonly reported in both treatment groups. [See Adverse Reactions (6.4).] Doses greater than 40 mg have not been studied in this population. Children and adolescent females of childbearing potential should be counseled on appropriate contraceptive methods while on pravastatin therapy [see Contraindications (4.3) and Use in Specific Populations (8.1)]. For dosing information [see Dosage and Administration (2.4)].

Double-blind, placebo-controlled pravastatin studies in children less than 8 years of age have not been conducted.

8.5 Geriatric Use

Two secondary prevention trials with pravastatin (CARE and LIPID) included a total of 6593 subjects treated with pravastatin 40 mg for periods ranging up to 6 years. Across these 2 studies, 36.1% of pravastatin subjects were aged 65 and older and 0.8% were aged 75 and older. The beneficial effect of pravastatin in elderly subjects in reducing cardiovascular events and in modifying lipid profiles was similar to that seen in younger subjects. The adverse event profile in the elderly was similar to that in the overall population. Other reported clinical experience has not identified differences in responses to pravastatin between elderly and younger patients.

Mean pravastatin AUCs are slightly (25%-50%) higher in elderly subjects than in healthy young subjects, but mean maximum plasma concentration (Cmax), time to maximum plasma concentration (Tmax), and half-life (t1/2) values are similar in both age groups and substantial accumulation of pravastatin would not be expected in the elderly [see Clinical Pharmacology (12.3)].

Since advanced age (≥65 years) is a predisposing factor for myopathy, Pravastatin Sodium should be prescribed with caution in the elderly [see Warnings and Precautions (5.1) and Clinical Pharmacology (12.3)].

8.6 Homozygous Familial Hypercholesterolemia

Pravastatin has not been evaluated in patients with rare homozygous familial hypercholesterolemia. In this group of patients, it has been reported that statins are less effective because the patients lack functional LDL receptors.

10 OVERDOSAGE

To date, there has been limited experience with overdosage of pravastatin. If an overdose occurs, it should be treated symptomatically with laboratory monitoring and supportive measures should be instituted as required.

11 DESCRIPTION

Pravastatin sodium is one of a class of lipid-lowering compounds, the statins, which reduce cholesterol biosynthesis. These agents are competitive inhibitors of HMG-CoA reductase, the enzyme catalyzing the early rate-limiting step in cholesterol biosynthesis, conversion of HMG-CoA to mevalonate.

Pravastatin sodium is designated chemically as 1-Naphthalene-heptanoic acid, 1,2,6,7,8,8a- hexahydro-2-methyl-8-(2-methyl-1-oxobutoxy)-β,δ,6-trihydroxy-,monosodium salt, [1S- [1α(βS*,δS*),2α,6α,8β(R*),8aα]]-.

Structural formula:

Pravastatin sodium is white to off-white powder. It is a relatively polar hydrophilic compound with a partition coefficient (n-octanol/water) of 0.59. It is soluble in water (676 mg/mL).

Pravastatin sodium is available for oral administration as 10 mg, 20 mg, 40 mg, and 80 mg tablets. Inactive ingredients include: Croscarmellose sodium, lactose Monohydrate, magnesium oxide, magnesium stearate, microcrystalline cellulose, and povidone.

12 CLINICAL PHARMACOLOGY

12.1 Mechanism of Action

Pravastatin is a reversible inhibitor of 3-hydroxy-3-methylglutaryl-coenzyme A (HMG-CoA) reductase, the enzyme that catalyzes the conversion of HMG-CoA to mevalonate, an early and rate limiting step in the biosynthetic pathway for cholesterol. In addition, pravastatin reduces VLDL and TG and increases HDL-C.

12.3 Pharmacokinetics

General

Absorption: Pravastatin Sodium is administered orally in the active form. In studies in man, peak plasma pravastatin concentrations occurred 1 to 1.5 hours upon oral administration. Based on urinary recovery of total radiolabeled drug, the average oral absorption of pravastatin is 34% and absolute bioavailability is 17%. While the presence of food in the gastrointestinal tract reduces systemic bioavailability, the lipid-lowering effects of the drug are similar whether taken with or 1 hour prior to meals.

Pravastatin plasma concentrations, including area under the concentration-time curve (AUC), Cmax, and steady-state minimum (Cmin), are directly proportional to administered dose. Systemic bioavailability of pravastatin administered following a bedtime dose was decreased 60% compared to that following an AM dose. Despite this decrease in systemic bioavailability, the efficacy of pravastatin administered once daily in the evening, although not statistically significant, was marginally more effective than that after a morning dose.

The coefficient of variation (CV), based on between-subject variability, was 50% to 60% for AUC. The geometric means of pravastatin Cmax and AUC following a 20 mg dose in the fasted state were 26.5 ng/mL and 59.8 ng*hr/mL, respectively.

Steady-state AUCs, Cmax, and Cmin plasma concentrations showed no evidence of pravastatin accumulation following once or twice daily administration of Pravastatin Sodium tablets.

Distribution: Approximately 50% of the circulating drug is bound to plasma proteins.

Metabolism: The major biotransformation pathways for pravastatin are: (a) isomerization to 6-epi pravastatin and the 3α-hydroxyisomer of pravastatin (SQ 31,906) and (b) enzymatic ring hydroxylation to SQ 31,945. The 3α-hydroxyisomeric metabolite (SQ 31,906) has 1/10 to 1/40 the HMG-CoA reductase inhibitory activity of the parent compound. Pravastatin undergoes extensive first-pass extraction in the liver (extraction ratio 0.66).

Excretion: Approximately 20% of a radiolabeled oral dose is excreted in urine and 70% in the feces. After intravenous administration of radiolabeled pravastatin to normal volunteers, approximately 47% of total body clearance was via renal excretion and 53% by non-renal routes (i.e., biliary excretion and biotransformation).

Following single dose oral administration of ^14C-pravastatin, the radioactive elimination t½ for pravastatin is 1.8 hours in humans.

Specific Populations

Renal Impairment: A single 20 mg oral dose of pravastatin was administered to 24 patients with varying degrees of renal impairment (as determined by creatinine clearance). No effect was observed on the pharmacokinetics of pravastatin or its 3α-hydroxyl isomeric metabolite (SQ 31,906). Compared to healthy subjects with normal renal function, patients with severe renal impairment had 69% and 37% higher mean AUC and Cmax values, respectively, and a 0.61 hour shorter t1/2 for the inactive enzymatic ring hydroxylation metabolite (SQ 31,945).

Hepatic Impairment: In a study comparing the kinetics of pravastatin in patients with biopsy confirmed cirrhosis (N=7) and normal subjects (N=7), the mean AUC varied 18-fold in cirrhotic patients and 5-fold in healthy subjects. Similarly, the peak pravastatin values varied 47-fold for cirrhotic patients compared to 6-fold for healthy subjects. [See Warnings and Precautions (5.3).]

Geriatric: In a single oral dose study using pravastatin 20 mg, the mean AUC for pravastatin was approximately 27% greater and the mean cumulative urinary excretion (CUE) approximately 19% lower in elderly men (65-75 years old) compared with younger men (19-31 years old). In a similar study conducted in women, the mean AUC for pravastatin was approximately 46% higher and the mean CUE approximately 18% lower in elderly women (65-78 years old) compared with younger women (18-38 years old). In both studies, Cmax, Tmax, and t1/2 values were similar in older and younger subjects. [See Use in Specific Populations (8.5).]

Pediatric: After 2 weeks of once-daily 20 mg oral pravastatin administration, the geometric means of AUC were 80.7 (CV 44%) and 44.8 (CV 89%) ng*hr/mL for children (8-11 years, N=14) and adolescents (12-16 years, N=10), respectively. The corresponding values for Cmax were 42.4 (CV 54%) and 18.6 ng/mL (CV 100%) for children and adolescents, respectively. No conclusion can be made based on these findings due to the small number of samples and large variability. [See Use in Specific Populations (8.4).]

Drug-Drug Interactions

Table 3: Effect of Coadministered Drugs on the Pharmacokinetics of Pravastatin
Cyclosporine 5 mg/kg single dose | 40 mg single dose | ↑282% | ↑327%
Clarithromycin 500 mg BID for 9 days | 40 mg OD for 8 days | ↑110% | ↑128%
Boceprevir 800 mg TID for 6 days | 40 mg single dose | ↑63% | ↑49%
Darunavir 600 mg BID/Ritonavir 100 mg BID for 7 days | 40 mg single dose | ↑81% | ↑63%
Colestipol 10 g single dose | 20 mg single dose | ↓47% | ↓53%
Cholestyramine 4 g single dose Administered simultaneously Administered 1 hour prior to cholestyramine Administered 4 hours after cholestyramine | 20 mg single dose | ↓40% ↑12% ↓12% | ↓39% ↑30% ↓6.8%
Cholestyramine 24 g OD for 4 weeks | 20 mg BID for 8 weeks 5 mg BID for 8 weeks 10 mg BID for 8 weeks | ↓51% ↓38% ↓18% | ↑4.9% ↑23% ↓33%
Fluconazole 200 mg IV for 6 days 200 mg PO for 6 days | 20 mg PO+10 mg IV 20 mg PO+10 mg IV | ↓34% ↓16% | ↓33% ↓16%
Kaletra 400 mg/100 mg BID for 14 days | 20 mg OD for 4 days | ↑33% | ↑26%
Verapamil IR 120 mg for 1 day and Verapamil ER 480 mg for 3 days | 40 mg single dose | ↑31% | ↑42%
Cimetidine 300 mg QID for 3 days | 20 mg single dose | ↑30% | ↑9.8%
Antacids 15 mL QID for 3 days | 20 mg single dose | ↓28% | ↓24%
Digoxin 0.2 mg OD for 9 days | 20 mg OD for 9 days | ↑23% | ↑26%
Probucol 500 mg single dose | 20 mg single dose | ↑14% | ↑24%
Warfarin 5 mg OD for 6 days | 20 mg BID for 6 days | ↓13% | ↑6.7%
Itraconazole 200 mg OD for 30 days | 40 mg OD for 30 days | ↑11%(compared to Day 1) | ↑17%(compared to Day 1)
Gemfibrozil 600 mg single dose | 20 mg single dose | ↓7.0% | ↓20%
Aspirin 324 mg single dose | 20 mg single dose | ↑4.7% | ↑8.9%
Niacin 1 g single dose | 20 mg single dose | ↓3.6% | ↓8.2%
Diltiazem | 20 mg single dose | ↑2.7% | ↑30%
Grapefruit juice | 40 mg single dose | ↓1.8% | ↑3.7%

BID = twice daily; OD = once daily; QID = four times daily

Table 4: Effect of Pravastatin on the Pharmacokinetics of Coadministered Drugs
Pravastatin Dosing Regimen | Name and Dose | Change in AUC | Change in Cmax
20 mg BID for 6 days | Warfarin 5 mg OD for 6 days Change in mean prothrombin time | ↑17% ↑0.4 sec | ↑15%
20 mg OD for 9 days | Digoxin 0.2 mg OD for 9 days | ↑4.6% | ↑5.3%
20 mg BID for 4 weeks 10 mg BID for 4 weeks 5 mg BID for 4 weeks | Antipyrine 1.2 g single dose | ↑3.0% ↑1.6% ↑Less than 1% | Not Reported
20 mg OD for 4 days | Kaletra 400 mg/100 mg BID for 14 days | No change | No change

BID = twice daily; OD = once daily

13 NONCLINICAL TOXICOLOGY

13.1 Carcinogenesis, Mutagenesis, Impairment of Fertility

In a 2-year study in rats fed pravastatin at doses of 10, 30, or 100 mg/kg body weight, there was an increased incidence of hepatocellular carcinomas in males at the highest dose (p<0.01). These effects in rats were observed at approximately 12 times the human dose (HD) of 80 mg based on body surface area (mg/m^2) and at approximately 4 times the HD, based on AUC.

In a 2-year study in mice fed pravastatin at doses of 250 and 500 mg/kg/day, there was an increased incidence of hepatocellular carcinomas in males and females at both 250 and 500 mg/kg/day (p<0.0001). At these doses, lung adenomas in females were increased (p=0.013). These effects in mice were observed at approximately 15 times (250 mg/kg/day) and 23 times (500 mg/kg/day) the HD of 80 mg, based on AUC. In another 2-year study in mice with doses up to 100 mg/kg/day (producing drug exposures approximately 2 times the HD of 80 mg, based on AUC), there were no drug-induced tumors.

No evidence of mutagenicity was observed in vitro, with or without rat-liver metabolic activation, in the following studies: microbial mutagen tests, using mutant strains of Salmonella typhimurium or Escherichia coli; a forward mutation assay in L5178Y TK +/− mouse lymphoma cells; a chromosomal aberration test in hamster cells; and a gene conversion assay using Saccharomyces cerevisiae. In addition, there was no evidence of mutagenicity in either a dominant lethal test in mice or a micronucleus test in mice.

In a fertility study in adult rats with daily doses up to 500 mg/kg, pravastatin did not produce any adverse effects on fertility or general reproductive performance.

13.2 Animal Toxicology and/or Pharmacology

CNS Toxicity

CNS vascular lesions, characterized by perivascular hemorrhage and edema and mononuclear cell infiltration of perivascular spaces, were seen in dogs treated with pravastatin at a dose of 25 mg/kg/day. These effects in dogs were observed at approximately 59 times the HD of 80 mg/day, based on AUC. Similar CNS vascular lesions have been observed with several other drugs in this class.

A chemically similar drug in this class produced optic nerve degeneration (Wallerian degeneration of retinogeniculate fibers) in clinically normal dogs in a dose-dependent fashion starting at 60 mg/kg/day, a dose that produced mean plasma drug levels about 30 times higher than the mean drug level in humans taking the highest recommended dose (as measured by total enzyme inhibitory activity). This same drug also produced vestibulocochlear Wallerian-like degeneration and retinal ganglion cell chromatolysis in dogs treated for 14 weeks at 180 mg/kg/day, a dose which resulted in a mean plasma drug level similar to that seen with the 60 mg/kg/day dose.

When administered to juvenile rats (postnatal days [PND] 4 through 80 at 5-45 mg/kg/day), no drug related changes were observed at 5 mg/kg/day. At 15 and 45 mg/kg/day, altered body- weight gain was observed during the dosing and 52-day recovery periods as well as slight thinning of the corpus callosum at the end of the recovery period. This finding was not evident in rats examined at the completion of the dosing period and was not associated with any inflammatory or degenerative changes in the brain. The biological relevance of the corpus callosum finding is uncertain due to the absence of any other microscopic changes in the brain or peripheral nervous tissue and because it occurred at the end of the recovery period.

Neurobehavioral changes (enhanced acoustic startle responses and increased errors in water- maze learning) combined with evidence of generalized toxicity were noted at 45 mg/kg/day during the later part of the recovery period. Serum pravastatin levels at 15 mg/kg/day are approximately 1 times (AUC) the maximum pediatric dose of 40 mg. No thinning of the corpus callosum was observed in rats dosed with pravastatin (250 mg/kg/day) beginning PND 35 for 3 months suggesting increased sensitivity in younger rats. PND 35 in a rat is approximately equivalent to an 8- to 12-year-old human child. Juvenile male rats given 90 times (AUC) the 40 mg dose had decreased fertility (20%) with sperm abnormalities compared to controls.

14 CLINICAL STUDIES

14.1 Prevention of Coronary Heart Disease

In the Pravastatin Primary Prevention Study (WOS),^3 the effect of Pravastatin Sodium on fatal and nonfatal CHD was assessed in 6595 men 45 to 64 years of age, without a previous MI, and with LDL-C levels between 156 to 254 mg/dL (4-6.7 mmol/L). In this randomized, double-blind, placebo-controlled study, patients were treated with standard care, including dietary advice, and either Pravastatin Sodium 40 mg daily (N=3302) or placebo (N=3293) and followed for a median duration of 4.8 years. Median (25th, 75th percentile) percent changes from baseline after 6 months of pravastatin treatment in Total-C, LDL-C, TG, and HDL-C were −20.3 (−26.9, −11.7),
−27.7 (−36.0, −16.9), −9.1 (−27.6, 12.5), and 6.7 (−2.1, 15.6), respectively.

Pravastatin Sodium significantly reduced the rate of first coronary events (either CHD death or nonfatal MI) by 31% (248 events in the placebo group [CHD death=44, nonfatal MI=204] versus 174 events in the Pravastatin Sodium group [CHD death=31, nonfatal MI=143], p=0.0001 [see figure below]). The risk reduction with Pravastatin Sodium was similar and significant throughout the entire range of baseline LDL cholesterol levels. This reduction was also similar and significant across the age range studied with a 40% risk reduction for patients younger than 55 years and a 27% risk reduction for patients 55 years and older. The Pravastatin Primary Prevention Study included only men, and therefore it is not clear to what extent these data can be extrapolated to a similar population of female patients.

Pravastatin Sodium also significantly decreased the risk for undergoing myocardial revascularization procedures (coronary artery bypass graft [CABG] surgery or percutaneous transluminal coronary angioplasty [PTCA]) by 37% (80 vs 51 patients, p=0.009) and coronary angiography by 31% (128 vs 90, p=0.007). Cardiovascular deaths were decreased by 32% (73 vs 50, p=0.03) and there was no increase in death from non-cardiovascular causes.

14.2 Secondary Prevention of Cardiovascular Events

In the LIPID^4 study, the effect of Pravastatin Sodium, 40 mg daily, was assessed in 9014 patients (7498 men; 1516 women; 3514 elderly patients [age ≥65 years]; 782 diabetic patients) who had experienced either an MI (5754 patients) or had been hospitalized for unstable angina pectoris (3260 patients) in the preceding 3 to 36 months. Patients in this multicenter, double-blind, placebo-controlled study participated for an average of 5.6 years (median of 5.9 years) and at randomization had Total-C between 114 and 563 mg/dL (mean 219 mg/dL), LDL-C between 46 and 274 mg/dL (mean 150 mg/dL), TG between 35 and 2710 mg/dL (mean 160 mg/dL), and HDL-C between 1 and 103 mg/dL (mean 37 mg/dL). At baseline, 82% of patients were receiving aspirin and 76% were receiving antihypertensive medication. Treatment with Pravastatin Sodium significantly reduced the risk for total mortality by reducing coronary death (see Table 5). The risk reduction due to treatment with Pravastatin Sodium on CHD mortality was consistent regardless of age. Pravastatin Sodium significantly reduced the risk for total mortality (by reducing CHD death) and CHD events (CHD mortality or nonfatal MI) in patients who qualified with a history of either MI or hospitalization for unstable angina pectoris.

Table 5: LIPID - Primary and Secondary Endpoints
 | Number (%) of Subjects
Event | Pravastatin 40 mg (N=4512) | Placebo (N=4502) | Risk Reduction | p-value
Primary Endpoint
CHD mortality | 287 (6.4) | 373 (8.3) | 24% | 0.0004
Secondary Endpoints
Total mortality | 498 (11.0) | 633 (14.1) | 23% | <0.0001
CHD mortality or nonfatal MI | 557 (12.3) | 715 (15.9) | 24% | <0.0001
Myocardial revascularization procedures (CABG or PTCA) | 584 (12.9) | 706 (15.7) | 20% | <0.0001
Stroke
All-cause | 169 (3.7) | 204 (4.5) | 19% | 0.0477
Non-hemorrhagic | 154 (3.4) | 196 (4.4) | 23% | 0.0154
Cardiovascular mortality | 331 (7.3) | 433 (9.6) | 25% | <0.0001

In the CARE^5 study, the effect of Pravastatin Sodium, 40 mg daily, on CHD death and nonfatal MI was assessed in 4159 patients (3583 men and 576 women) who had experienced a MI in the preceding 3 to 20 months and who had normal (below the 75th percentile of the general population) plasma total cholesterol levels. Patients in this double-blind, placebo-controlled study participated for an average of 4.9 years and had a mean baseline Total-C of 209 mg/dL. LDL-C levels in this patient population ranged from 101 to 180 mg/dL (mean 139 mg/dL). At baseline, 84% of patients were receiving aspirin and 82% were taking antihypertensive medications. Median (25th, 75th percentile) percent changes from baseline after 6 months of pravastatin treatment in Total-C, LDL-C, TG, and HDL-C were −22.0 (−28.4, −14.9), −32.4 (−39.9, −23.7), −11.0 (−26.5, 8.6), and 5.1 (−2.9, 12.7), respectively. Treatment with Pravastatin Sodium significantly reduced the rate of first recurrent coronary events (either CHD death or nonfatal MI), the risk of undergoing revascularization procedures (PTCA, CABG), and the risk for stroke or TIA (see Table 6).

Table 6: CARE - Primary and Secondary Endpoints
 | Number (%) of Subjects
Event | Pravastatin 40 mg (N=2081) | Placebo (N=2078) | Risk Reduction | p-value
Primary Endpoint
CHD mortality or nonfatal MI [The risk reduction due to treatment with Pravastatin Sodium was consistent in both sexes.] | 212 (10.2) | 274 (13.2) | 24% | 0.003
Secondary Endpoints
Myocardial revascularization procedures (CABG or PTCA) | 294 (14.1) | 391 (18.8) | 27% | <0.001
Stroke or TIA | 93 (4.5) | 124 (6.0) | 26% | 0.029

In the PLAC I^6 study, the effect of pravastatin therapy on coronary atherosclerosis was assessed by coronary angiography in patients with coronary disease and moderate hypercholesterolemia (baseline LDL-C range: 130-190 mg/dL). In this double-blind, multicenter, controlled clinical trial, angiograms were evaluated at baseline and at 3 years in 264 patients. Although the difference between pravastatin and placebo for the primary endpoint (per-patient change in mean coronary artery diameter) and 1 of 2 secondary endpoints (change in percent lumen diameter stenosis) did not reach statistical significance, for the secondary endpoint of change in minimum lumen diameter, statistically significant slowing of disease was seen in the pravastatin treatment group (p=0.02).

In the REGRESS^7 study, the effect of pravastatin on coronary atherosclerosis was assessed by coronary angiography in 885 patients with angina pectoris, angiographically documented coronary artery disease, and hypercholesterolemia (baseline total cholesterol range: 160-310 mg/dL). In this double-blind, multicenter, controlled clinical trial, angiograms were evaluated at baseline and at 2 years in 653 patients (323 treated with pravastatin). Progression of coronary atherosclerosis was significantly slowed in the pravastatin group as assessed by changes in mean segment diameter (p=0.037) and minimum obstruction diameter (p=0.001).

Analysis of pooled events from PLAC I, PLAC II,^8 REGRESS, and KAPS^9 studies (combined N=1891) showed that treatment with pravastatin was associated with a statistically significant reduction in the composite event rate of fatal and nonfatal MI (46 events or 6.4% for placebo versus 21 events or 2.4% for pravastatin, p=0.001). The predominant effect of pravastatin was to reduce the rate of nonfatal MI.

14.3 Primary Hypercholesterolemia (Fredrickson Types IIa and IIb)

Pravastatin Sodium is highly effective in reducing Total-C, LDL-C, and TG in patients with heterozygous familial, presumed familial combined, and non-familial (non-FH) forms of primary hypercholesterolemia, and mixed dyslipidemia. A therapeutic response is seen within 1 week, and the maximum response usually is achieved within 4 weeks. This response is maintained during extended periods of therapy. In addition, Pravastatin Sodium is effective in reducing the risk of acute coronary events in hypercholesterolemic patients with and without previous MI.

A single daily dose is as effective as the same total daily dose given twice a day. In multicenter, double-blind, placebo-controlled studies of patients with primary hypercholesterolemia, treatment with pravastatin in daily doses ranging from 10 to 40 mg consistently and significantly decreased Total-C, LDL-C, TG, and Total-C/HDL-C and LDL-C/HDL-C ratios (see Table 7).

In a pooled analysis of 2 multicenter, double-blind, placebo-controlled studies of patients with primary hypercholesterolemia, treatment with pravastatin at a daily dose of 80 mg (N=277) significantly decreased Total-C, LDL-C, and TG. The 25th and 75th percentile changes from baseline in LDL-C for pravastatin 80 mg were −43% and −30%. The efficacy results of the individual studies were consistent with the pooled data (see Table 7).

Treatment with Pravastatin Sodium modestly decreased VLDL-C and Pravastatin Sodium across all doses produced variable increases in HDL-C (see Table 7).

Table 7: Primary Hypercholesterolemia Studies: Dose Response of Pravastatin Sodium Once Daily Administration
Dose | Total-C | LDL-C | HDL-C | TG
Mean Percent Changes From Baseline After 8 Weeks [A multicenter, double-blind, placebo-controlled study.]
Placebo (N=36) | −3% | −4% | +1% | −4%
10mg (N=18) | −16% | −22% | +7% | −15%
20mg (N=19) | −24% | −32% | +2% | −11%
40mg (N=18) | −25% | −34% | +12% | −24%
Mean Percent Changes From Baseline After 6 Weeks [Pooled analysis of 2 multicenter, double-blind, placebo-controlled studies.]
Placebo (N=162) | 0% | −1% | -1% | +1%
80mg (N=277) | −27% | −37% | +3% | −19%

In another clinical trial, patients treated with pravastatin in combination with cholestyramine (70% of patients were taking cholestyramine 20 or 24 g per day) had reductions equal to or greater than 50% in LDL-C. Furthermore, pravastatin attenuated cholestyramine-induced increases in TG levels (which are themselves of uncertain clinical significance).

14.4 Hypertriglyceridemia (Fredrickson Type IV)

The response to pravastatin in patients with Type IV hyperlipidemia (baseline TG >200 mg/dL and LDL-C <160 mg/dL) was evaluated in a subset of 429 patients from the CARE study. For pravastatin-treated subjects, the median (min, max) baseline TG level was 246.0 (200.5, 349.5) mg/dL (see Table 8).

Table 8: Patients with Fredrickson Type IV Hyperlipidemia Median (25th, 75th percentile) % Change from Baseline
 | Pravastatin 40 mg (N=429) | Placebo (N=430)
TG | −21.1 (−34.8, 1.3) | −6.3 (−23.1, 18.3)
Total-C | −22.1 (−27.1, −14.8) | 0.2 (−6.9, 6.8)
LDL-C | −31.7 (−39.6, −21.5) | 0.7 (−9.0, 10.0)
HDL-C | 7.4 (−1.2, 17.7) | 2.8 (−5.7, 11.7)
Non-HDL-C | −27.2 (−34.0, −18.5) | −0.8 (−8.2, 7.0)

14.5 Dysbetalipoproteinemia(Fredrickson Type III)

The response to pravastatin in two double-blind crossover studies of 46 patients with genotype E2/E2 and Fredrickson Type III dysbetalipoproteinemia is shown in Table 9.

Table 9: Patients with FredricksonType III Dysbetalipoproteinemia Median (min,max) % Change from Baseline

 | Median (min, max) at Baseline (mg/dL) | Median % Change(min, max) Pravastatin 40 mg (N=20)
Study 1
Total-C | 386.5 (245.0, 672.0) | −32.7 (−58.5, 4.6)
TG | 443.0 (275.0, 1299.0) | −23.7 (−68.5, 44.7)
VLDL-Ca | 206.5 (110.0, 379.0) | −43.8 (−73.1, −14.3)
LDL-Ca | 117.5 (80.0,170.0) | −40.8 (−63.7, 4.6)
HDL-C | 30.0 (18.0,88.0) | 6.4 (−45.0,105.6)
Non-HDL-C | 344.5 (215.0, 646.0) | −36.7 (−66.3, 5.8)
a N=14
 | Median (min, max) at Baseline (mg/dL) | Median % Change(min, max) Pravastatin 40 mg (N=26)
Study 2
Total-C | 340.3 (230.1, 448.6) | −31.4 (−54.5, −13.0)
TG | 343.2 (212.6, 845.9) | −11.9 (−56.5, 44.8)
VLDL-C | 145.0 (71.5,309.4) | −35.7 (−74.7, 19.1)
LDL-C | 128.6 (63.8,177.9) | −30.3 (−52.2, 13.5)
HDL-C | 38.7 (27.1,58.0) | 5.0 (−17.7, 66.7)
Non-HDL-C | 295.8 (195.3, 421.5) | −35.5 (−81.0, −13.5)

14.6 Pediatric Clinical Study

A double-blind, placebo-controlled study in 214 patients (100 boys and 114 girls) with heterozygous familial hypercholesterolemia (HeFH), aged 8 to 18 years was conducted for 2 years. The children (aged 8-13 years) were randomized to placebo (N=63) or 20 mg of pravastatin daily (N=65) and the adolescents (aged 14-18 years) were randomized to placebo (N=45) or 40 mg of pravastatin daily (N=41). Inclusion in the study required an LDL-C level >95th percentile for age and sex and one parent with either a clinical or molecular diagnosis of familial hypercholesterolemia. The mean baseline LDL-C value was 239 mg/dL and 237 mg/dL in the pravastatin (range: 151-405 mg/dL) and placebo (range: 154-375 mg/dL) groups, respectively.

Pravastatin significantly decreased plasma levels of LDL-C, Total-C, and ApoB in both children and adolescents (see Table 10). The effect of pravastatin treatment in the 2 age groups was similar.

Table 10: Lipid-Lowering Effects of Pravastatin in Pediatric Patients with Heterozygous Familial Hypercholesterolemia: Least-Squares Mean % Change from Baseline at Month 24 (Last Observation Carried Forward: Intent-to-Treat) [The above least-squares mean values were calculated based on log-transformed lipid values.]
 | Pravastatin 20 mg (Aged 8-13 years) N=65 | Pravastatin 40 mg (Aged 14-18 years) | Combined Pravastatin (Aged 8-18 years) N=106 | Combined Placebo (Aged 8-18 years) N=108 | 95% CI of the Difference Between Combined Pravastatin and Placebo
LDL-C | −26.04 | −21.07 | −24.07 | −1.52 | (−26.74, −18.86)
TC | −20.75 | −13.08 | −17.72 | −0.65 | (−20.40, −13.83)
HDL-C | 1.04 | 13.71 | 5.97 | 3.13 | (−1.71, −7.43)
TG | −9.58 | −0.30 | −5.88 | −3.27 | (−13.95, 10.01)
ApoB (N) | −23.16 (61) [Significant at p≤0.0001 when compared with placebo.] | −18.08 (39) | −21.11 (100) | −0.97 (106) | (−24.29, −16.18)

The mean achieved LDL-C was 186 mg/dL (range: 67-363 mg/dL) in the pravastatin group compared to 236 mg/dL (range: 105-438 mg/dL) in the placebo group.

The safety and efficacy of pravastatin doses above 40 mg daily have not been studied in children. The long-term efficacy of pravastatin therapy in childhood to reduce morbidity and mortality in adulthood has not been established.

15 REFERENCES

1. Fredrickson DS, Levy RI, Lees RS. Fat transport in lipoproteins - An integrated approach to mechanisms and disorders. N Engl J Med. 1967;276: 34-44, 94-103, 148-156, 215-225, 273-281.
2. Manson JM, Freyssinges C, Ducrocq MB, Stephenson WP. Postmarketing surveillance of lovastatin and simvastatin exposure during pregnancy. Reprod Toxicol. 1996;10(6):439-446.
3. Shepherd J, Cobbe SM, Ford I, et al, for the West of Scotland Coronary Prevention Study Group (WOS). Prevention of coronary heart disease with pravastatin in men with hypercholesterolemia. N Engl J Med. 1995;333:1301-1307.
4. The Long-term Intervention with Pravastatin in Ischemic Disease Group (LIPID). Prevention of cardiovascular events and death with pravastatin in patients with coronary heart disease and a broad range of initial cholesterol levels. N Engl J Med. 1998;339:1349-1357.
5. Sacks FM, Pfeffer MA, Moye LA, et al, for the Cholesterol and Recurrent Events Trial Investigators (CARE). The effect of pravastatin on coronary events after myocardial infarction in patients with average cholesterol levels. N Engl J Med. 1996;335:1001-1009.
6. Pitt B, Mancini GBJ, Ellis SG, et al, for the PLAC I Investigators. Pravastatin limitation of atherosclerosis in the coronary arteries (PLAC I): Reduction in atherosclerosis progression and clinical events. J Am Coll Cardiol. 1995;26:1133-1139.
7. Jukema JW, Bruschke AVG, van Boven AJ, et al, for the Regression Growth Evaluation Statin Study Group (REGRESS). Effects of lipid lowering by pravastatin on progression and regression of coronary artery disease in symptomatic man with normal to moderately elevated serum cholesterol levels. Circ. 1995;91:2528-2540.
8. Crouse JR, Byington RP, Bond MG, et al. Pravastatin, lipids, and atherosclerosis in the carotid arteries: Design features of a clinical trial with carotid atherosclerosis outcome (PLAC II). Control Clin Trials. 1992;13:495-506.
9. Salonen R, Nyyssonen K, Porkkala E, et al. Kuopio Atherosclerosis Prevention Study (KAPS). A population-based primary preventive trial of the effect of LDL lowering on atherosclerotic progression in carotid and femoral arteries. Circ. 1995;92:1758-1764.

16 HOW SUPPLIED/STORAGE AND HANDLING

16.1 How Supplied

Pravastatin Sodium Tablets, USP are supplied as:

40 mg tablets: White to off-white, rounded, rectangular-shaped, biconvex tablets debossed with “B 40” on one side and plain on other side.

- NDC 72162-1953-0: 1000 Tablets in a BOTTLE

16.2 Storage

Store at 25°C (77°F); excursions permitted to 15°C to 30°C (59°F to 86°F) [see USP Controlled Room Temperature]. Keep tightly closed (protect from moisture). Protect from light.

Repackaged/Relabeled by:
Bryant Ranch Prepack, Inc.
Burbank, CA 91504

17 PATIENT COUNSELING INFORMATION

Muscle Pain

Patients should be advised to report promptly unexplained muscle pain, tenderness or weakness, particularly if accompanied by malaise or fever or if these muscle signs or symptoms persist after discontinuing Pravastatin Sodium [see Warnings and Precautions (5.1)].

Liver Enzymes

It is recommended that liver enzyme tests be performed before the initiation of Pravastatin Sodium, and thereafter when clinically indicated. All patients treated with Pravastatin Sodium should be advised to promptly report any symptoms that may indicate liver injury, including fatigue, anorexia, right upper abdominal discomfort, dark urine, or jaundice [see Warnings and Precautions (5.3)].

Embryofetal Toxicity

Advise females of reproductive potential of the risk to a fetus, to use effective contraception during treatment, and to inform their healthcare provider of a known or suspected pregnancy [see Contraindications (4.3), Use in Specific Populations (8.1,8.3)].

Lactation

Advise women not to breastfeed during treatment with Pravastatin Sodium [see Contraindications (4.4), Use in Specific Populations (8.2)].

Manufactured by:

Appco Pharma LLC
Piscataway, NJ 08854

Manufactured for:

Biocon Pharma Inc.,
485 US Highway 1 S
Suite B305, Iselin
NJ 08830-3009

USA

Revised: 10/2020

PACKAGE LABEL

Pravastatin Sodium 40mg Tablet